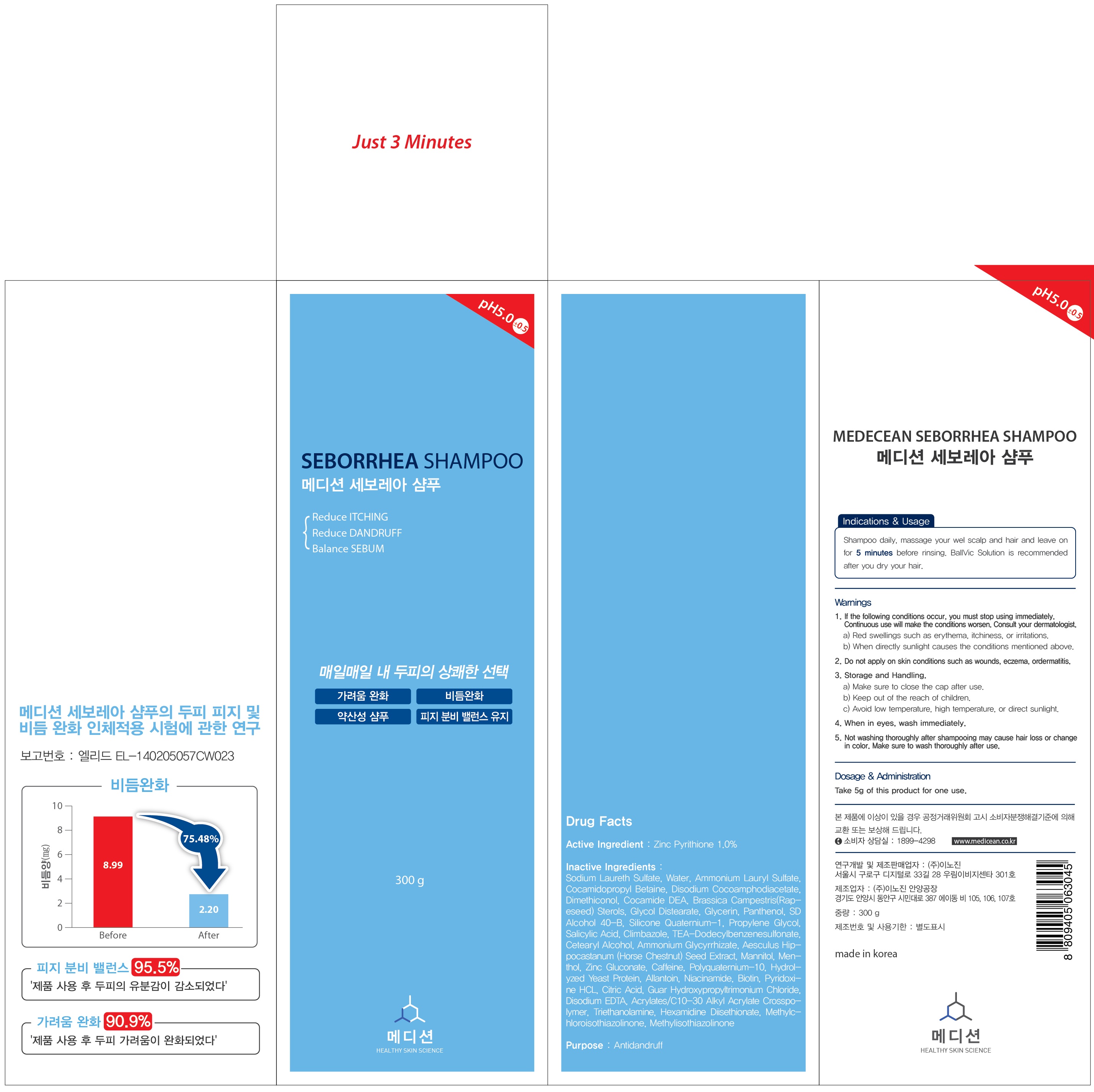 DRUG LABEL: MEDECEAN SEBORRHEA
NDC: 70540-010 | Form: SHAMPOO
Manufacturer: INNOGENE CO.,LTD
Category: otc | Type: HUMAN OTC DRUG LABEL
Date: 20160321

ACTIVE INGREDIENTS: PYRITHIONE ZINC 3.0 g/300 g
INACTIVE INGREDIENTS: Water; Ammonium Lauryl Sulfate

ACTIVE INGREDIENT

Active Ingredient: Zinc Pyrithione 1.0%

INACTIVE INGREDIENT

Inactive Ingredients: Sodium Laureth Sulfate, Water, Ammonium Lauryl Sulfate, Cocamidopropyl Betaine, Disodium Cocoamphodiacetate, Dimethiconol, Cocamide DEA, Brassica Campestris (Rapeseed) Sterols, Glycol Distearate, Glycerin, Panthenol, SD Alcohol 40-B, Silicone Quaternium-1, Propylene Glycol, Salicylic Acid, Climbazole, TEA-Dodecylbenzenesulfonate, Cetearyl Alcohol, Ammonium Glycyrrhizate, Aesculus Hippocastanum (Horse Chestnut) Seed Extract, Mannitol, Menthol, Zinc Gluconate, Caffeine, Polyquaternium-10, Hydrolyzed Yeast Protein, Allantoin, Niacinamide, Biotin, Pyridoxine HCL, Citric Acid, Guar Hydroxypropyltrimonium Chloride, Disodium EDTA, Acrylates/C10-30 Alkyl Acrylate Crosspolymer, Triethanolamine, Hexamidine Diisethionate, Methylchloroisothiazolinone, Methylisothiazolinone

PURPOSE

Purpose: Antidandruff

WARNINGS

Warnings: 1. If the following conditions occur, you must stop using immediately. Continuous use will make the conditions worsen. Consult your dermatologist. a. Red swellings such as erythema, itchiness, or irritations. b. When directly sunlight causes the conditions mentioned above. 2. Do not apply on skin conditions such as wounds, eczema, ordermatitis. 3. Storage and Handling. a. Make sure to close the cap after use. b. Keep out of the reach of children. c. Avoid low temperature, high temperature, or direct sunlight. 4. When in eyes, wash immediately. 5. Not washing thoroughly after shampooing may cause hair loss or change in color. Make sure to wash thoroughly after use.

KEEP OUT OF REACH OF CHILDREN

INDICATIONS & USAGE

Indications & Usage: Shampoo daily, massage your wel scalp and hair and leave on for 5 minutes before rinsing. BallVic Solution is recommended after you dry your hair.

DOSAGE & ADMINISTRATION

Dosage & Administration: Take 5g of this product for one use.